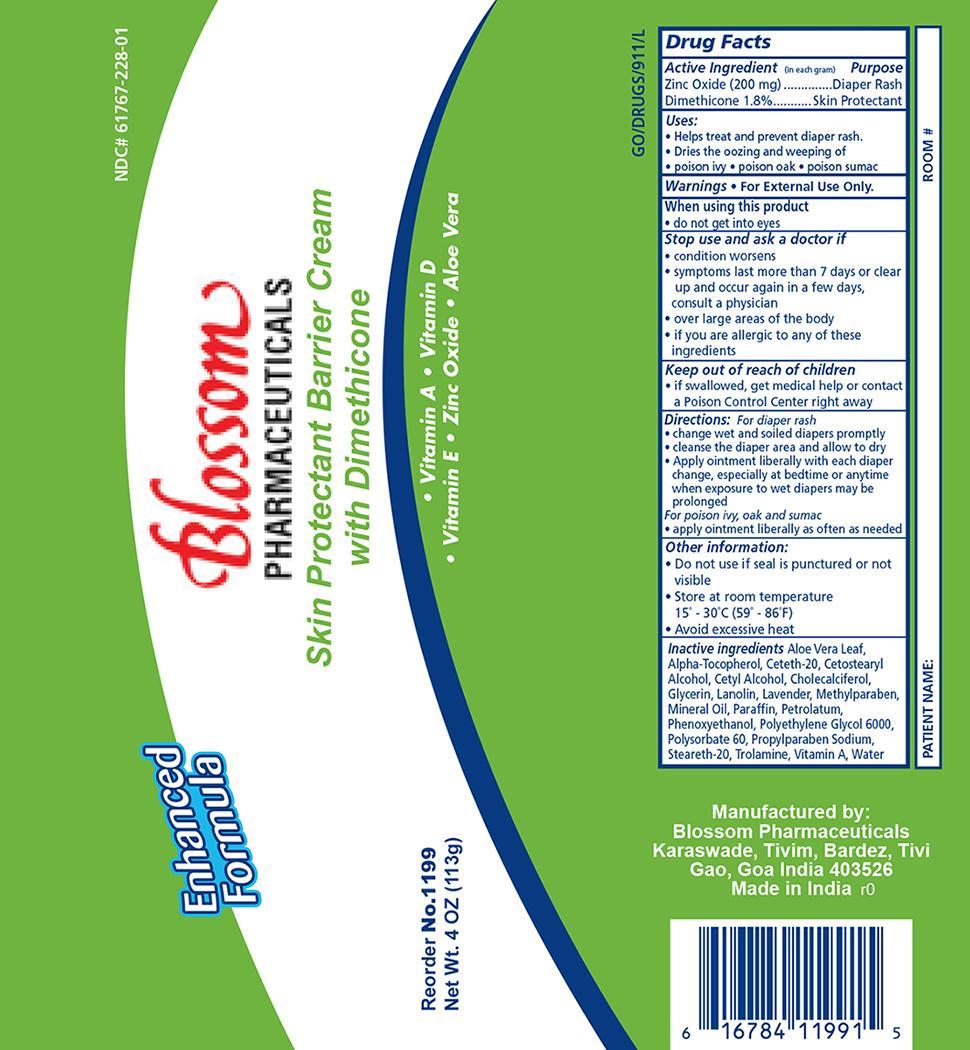 DRUG LABEL: Dyna1199 with Dimethicone
NDC: 61767-228 | Form: OINTMENT
Manufacturer: Blossom Pharmaceuticals
Category: otc | Type: HUMAN OTC DRUG LABEL
Date: 20141023

ACTIVE INGREDIENTS: ZINC OXIDE 2 g/100 g; DIMETHICONE 1.8 g/100 g
INACTIVE INGREDIENTS: LANOLIN; CETETH-20; MINERAL OIL; METHYLPARABEN; PROPYLPARABEN; GLYCERIN; CETYL ALCOHOL; CETOSTEARYL ALCOHOL; CHOLECALCIFEROL; VITAMIN A; ALPHA-TOCOPHEROL; ALOE VERA LEAF; PETROLATUM; TROLAMINE; WATER

Dyna1199 with Dimethicone Ointment

Active Ingredient Purpose

Zinc Oxide 2% Diaper Rash

Dimethicone 1.8% Skin Protectant

Purpose:

- Helps treat and prevent diaper rash
- Dries the oozing and weeping of;
- poison ivy
- poison oak
- poison sumac

Warnings:

For External Use Only.

When using this product:

Do not get in eyes.

Stop use and ask a doctor if:

- condition worsens
- symptoms last more than 7 days or clear up and occur again in a few days, consult a physician
- over large areas of the body
- if you are allergic to any of these ingredients

Keep out of reach of children.

If swallowed, get medical help or contact a Poison Control Center right away.

Dosage and Administration:

For poison ivy, oak and sumac:

- Apply ointment liberally as often as needed

For diaper Rash:

- change wet and soiled diapers promptly
- clean the diaper area and allow to dry
- apply ointment liberally with each diaper change, especially at bedtime or anytime when exposure to wet diapers may be prolonged.

Other information:

- Do not use if seal is punctured or not visible
- Store at room temperature 15^0 - 30^0 C (59^0 - 86^0 F)
- avoid excessive heat
- contains color additives including FDC yellow # 5 (Tartrazine)

INDICATIONS AND USAGE

Indications: For use as a general skin protectant and diaper rash.

Inactive ingredients:

Aloe Vera Leaf, Alpha-Tocopherol, Ceteth-20, Cetostearyl Alcohol, Cetyl Alcohol, Cholecalciferol, Glycerin, Lanolin, Lavender perfume, Methylparaben, Mineral Oil, Petrolatum, Propylparaben, Trolamine, Vitamin A, Water

Principal Display Panel

DynaShield Skin Protectant

DynaDi1199.jpg